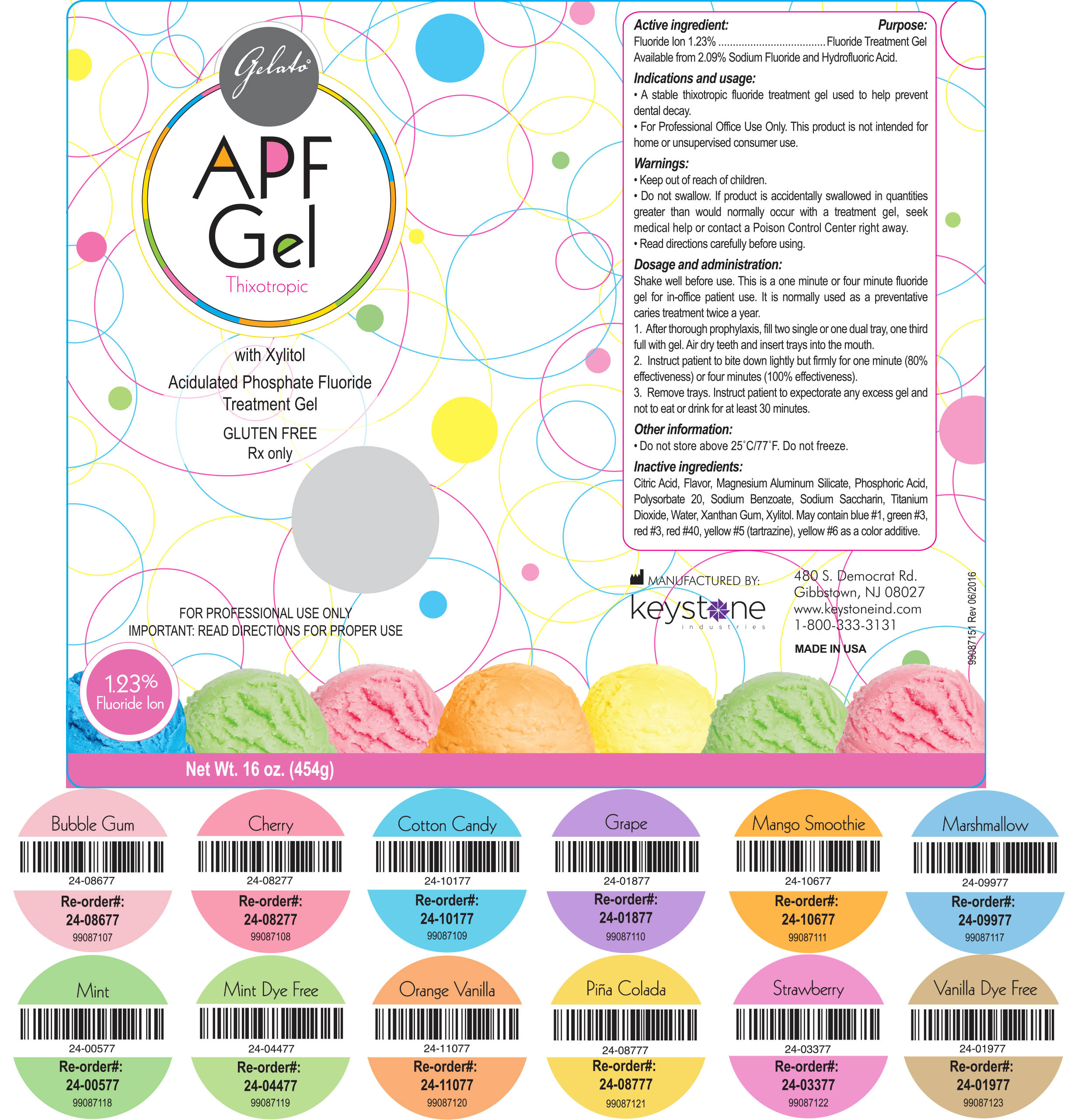 DRUG LABEL: Gelato APF
NDC: 68400-313 | Form: GEL
Manufacturer: Mycone Dental Supply Co., Inc DBA Keystone Industries and Deepak Products Inc.
Category: prescription | Type: HUMAN PRESCRIPTION DRUG LABEL
Date: 20240419

ACTIVE INGREDIENTS: SODIUM FLUORIDE 5.6 g/454 g
INACTIVE INGREDIENTS: CITRIC ACID MONOHYDRATE; MAGNESIUM ALUMINUM SILICATE; PHOSPHORIC ACID; POLYSORBATE 20; SODIUM BENZOATE; SACCHARIN SODIUM; TITANIUM DIOXIDE; WATER; XANTHAN GUM; XYLITOL; FD&C BLUE NO. 1; FD&C GREEN NO. 3; FD&C RED NO. 3; FD&C RED NO. 40; FD&C YELLOW NO. 5; FD&C YELLOW NO. 6

Active ingredient: Purpose:

Fluoride Ion 1.23% ............................ Fluoride Treatment Gel
Available from 2.09% Sodium Fluoride and Hydrofluoric Acid.

Indications and usage:

- A stable thixotropic fluoride treatment gel used to help prevent dental decay.
- For Professional Office Use Only. This product is not intended for home or unsupervised consumer use.

Warnings:

- Keep out of reach of children.
- Do not swallow. If product is accidentally swallowed in quantities greater than would normally occur with a treatment gel, seek medical help or contact a Poison Control Center right away.
- Read directions carefully before using.

Dosage and administration:

Shake well before use. This is a one minute or four minute fluoride gel for in-office patient use. It is normally used as a preventative caries treatment twice a year.

1. After thorough prophylaxis, fill two single or one dual tray, one third full with gel. Air dry teeth and insert trays into the mouth.

2. Instruct patient to bite down lightly but firmly for one minute (80% effectiveness) or four minutes (100% effectiveness).

3. Remove trays. Instruct patient to expectorate any excess gel and not to eat or drink for at least 30 minutes.

Inactive ingredients:

Citric Acid, Flavor, Magnesium Aluminum Silicate, Phosphoric Acid, Polysorbate 20, Sodium Benzoate, Sodium Saccharin, Titanium Dioxide, Water, Xantham Gum, Xylitol. May contain blue #1, green #3, red #3, red #40, yellow #5 (tartrazine), yellow #6 as a color additive.

Other information:

• Do not store above 25°C/77°F. Do not freeze.